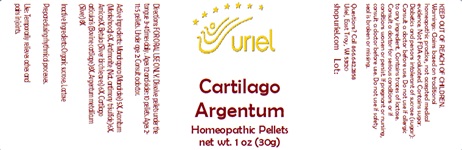 DRUG LABEL: Cartilago Argentum
NDC: 48951-3232 | Form: PELLET
Manufacturer: Uriel Pharmacy Inc.
Category: homeopathic | Type: HUMAN OTC DRUG LABEL
Date: 20241206

ACTIVE INGREDIENTS: BETULA PUBESCENS BARK 6 [hp_X]/1 1; SILVER 8 [hp_X]/1 1; MANDRAGORA OFFICINARUM ROOT 5 [hp_X]/1 1; ARNICA MONTANA FLOWER 6 [hp_X]/1 1; ACONITUM NAPELLUS 6 [hp_X]/1 1; ANTIMONY TRISULFIDE 6 [hp_X]/1 1; BOS TAURUS CARTILAGE 8 [hp_X]/1 1
INACTIVE INGREDIENTS: SUCROSE; LACTOSE, UNSPECIFIED FORM

Cartilago Argentum

INDICATIONS AND USAGE

Directions: FOR ORAL USE ONLY.

DOSAGE AND ADMINISTRATION

Dissolve pellets under the tongue 3-4 times daily. Ages 12 and older: 10 pellets. Ages 2-11: 5 pellets. Under age 2: Consult a doctor.

ACTIVE INGREDIENT

Active Ingredients: Mandragora (Mandrake) 5X, Aconitum (Monkshood) 6X, Antimonite (Nat. antimony trisulfide) 6X, Arnica 6X, Betula (Silver birch leaves) 6X, Cartilago articularis (Bovine cartilage) 8X, Argentum metallicum (Silver) 8X

Inactive Ingredients: Organic sucrose, Lactose

Prepared using rhythmical processes.

PURPOSE

Use: Temporarily relieves aches and pains in joints.

KEEP OUT OF REACH OF CHILDREN.

WARNINGS

Warnings: Claims based on traditional homeopathic practice, not accepted medical evidence. Not FDA evaluated. Contains sugar. Diabetics and persons intolerant of sucrose (sugar): Consult a doctor before use. Do not use if allergic to any ingredient. Contains traces of lactose. Consult a doctor for serious conditions or if conditions worsen or persist. If pregnant or nursing, consult a doctor before use. Do not use if safety seal is broken or missing.

Questions? Call 866.642.2858
Uriel, East Troy, WI 53120
shopuriel.com Lot: